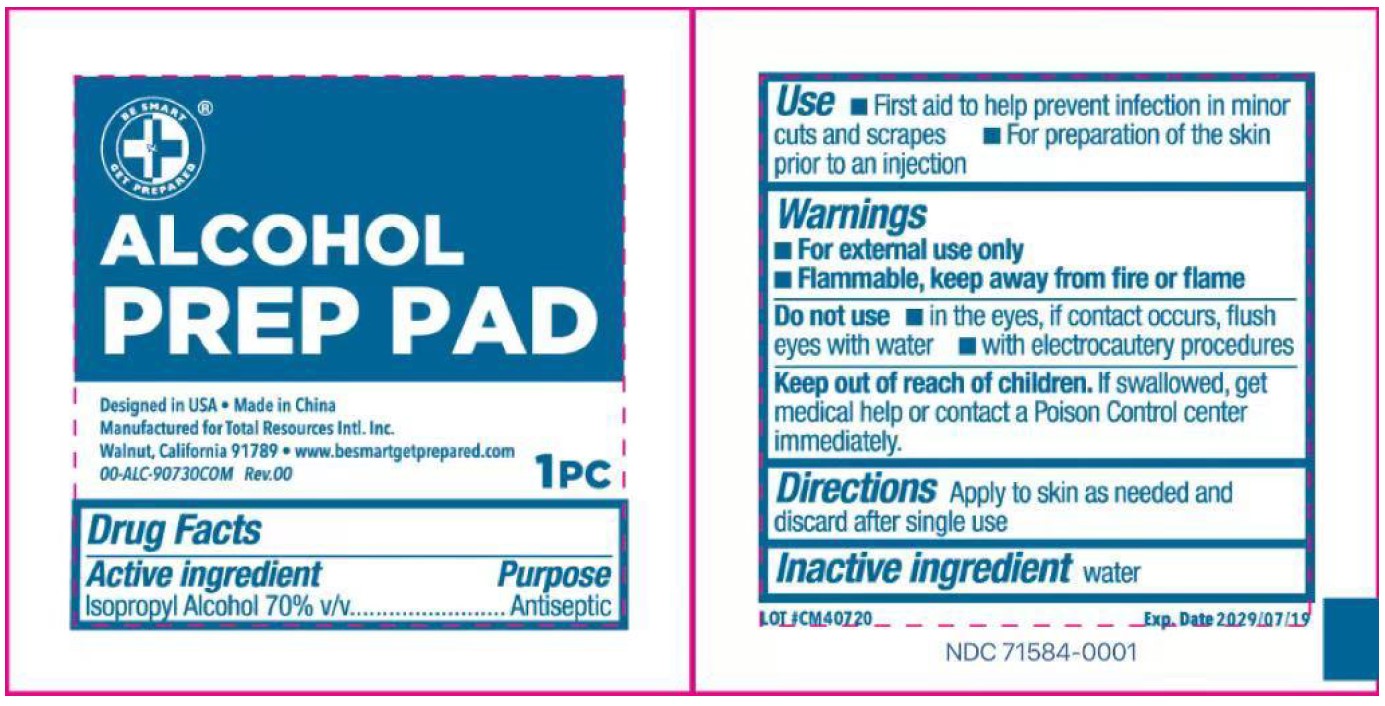 DRUG LABEL: ALCOHOL PREP PAD
NDC: 71584-0001 | Form: SWAB
Manufacturer: Guangdong Comfort Medical Products Co., Ltd.
Category: otc | Type: HUMAN OTC DRUG LABEL
Date: 20251019

ACTIVE INGREDIENTS: ISOPROPYL ALCOHOL 0.7 mL/1 mL
INACTIVE INGREDIENTS: WATER

ALCOHOL PREP PAD

ACTIVE INGREDIENT

Isopropyl Alcohol USP, 70% v/v

INACTIVE INGREDIENT

Water

PURPOSE

Antiseptic

KEEP OUT OF REACH OF CHILDREN

If swallowed, get medical help or contact a Poison Control Center immediately

INDICATIONS AND USAGE

For preparation of skin prior to injection; to decrease germs in minor cuts and scrapes

WARNINGS

For external use only. Flammable, keep away from fire and flame.

DOSAGE AND ADMINISTRATION

Wipe injection site vigorously

PACKAGE LABEL

Purpose: Antiseptic

Keep out of reach of children: If swallowed, get medical help or contact a Poison Control Center immediately.

Use: For preparation of skin prior to injection; to decrease germs in minor cuts and scrapes.

Warning: For external use only. Flammable, keep away from fire and flame.

Directions: Wipe injection site vigorously.

Inactive ingredients: Water

Active Ingredients: Isopropyl Alcohol USP, 70% v/v

Caution: Don’t apply to a irritated skin. Don,t use in the eyes, or on mucous membranes. In case of deep orpuncture wounds, consult a doctor.

Other information: Store at room temperature.